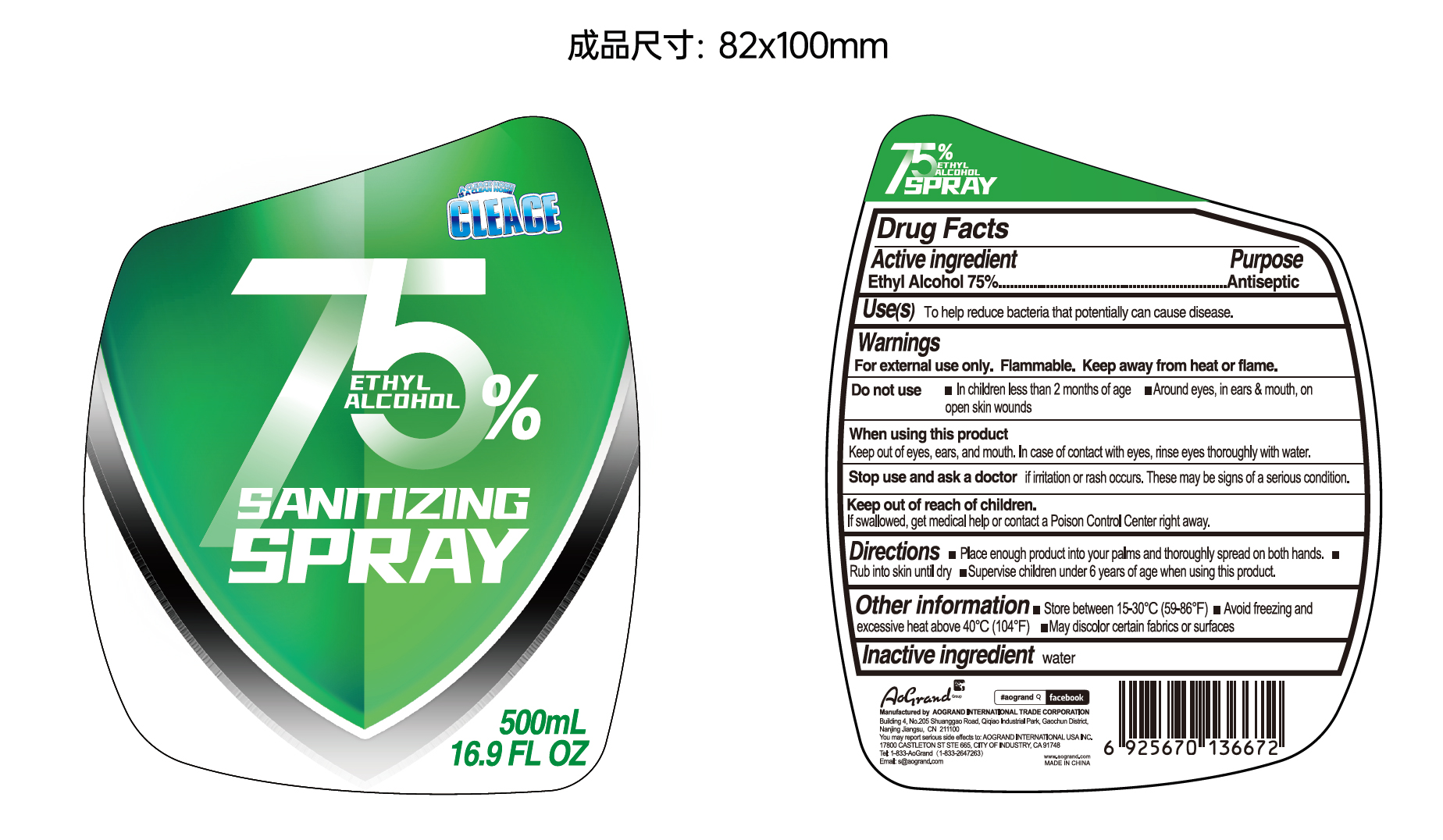 DRUG LABEL: CLEACE Alcohol disinfectant
NDC: 74621-015 | Form: LIQUID
Manufacturer: Aogrand International Trade Corporation
Category: otc | Type: HUMAN OTC DRUG LABEL
Date: 20230211

ACTIVE INGREDIENTS: ALCOHOL 75 mL/100 mL
INACTIVE INGREDIENTS: WATER

CLEACE Alcohol disinfectant

Active Ingredient

Ethyl Alcohol 75% v/v. Purpose: Antiseptic

Purpose

Antiseptic

Uses

To help reduce bacteria that potentially can cause disesase

Warnings

For external use only. Flammable. Keep away from fire or flame.

Do not use

- In children less than 2 months of age
- Around eyes, in ears & mouth, on open skin wounds

When using this product

Keep out of eyes, ears, and mouth. In case of contact with eyes, rinse eyes thoroughly with water.

Stop use and ask a doctor

if irritation or rash occurs. These may be signs of a serious condition.

Keep out of reach of children.

If swallowed, get medical help or contact a Poison Control Center right away.

Directions

- Place enough product into your palms and thoroughly spread on both hands.
- Rub into skin until dry.
- Supervise children under 6 years of age when using this product.

Other information

- Store between 15-30C (59-86F)
- Avoid freezing and excessive heat above 40C (104F)
- May discolor certain fabrics or surfaces.

Inactive ingredients

Water

Package Label - Principal Display Panel

500 mL NDC: 74621-015-01

A CLEACE HOME

IS A CLEAN HOME

CLEACE

75%

SANITIZING

DISINFECTANT

500mL

16.9 FL OZ